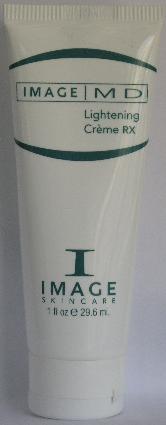 DRUG LABEL: Image MD Lightening Rx
NDC: 62742-4046 | Form: CREAM
Manufacturer: Allure Labs, Inc.
Category: otc | Type: HUMAN OTC DRUG LABEL
Date: 20100729

ACTIVE INGREDIENTS: HYDROQUINONE 40 mg/1 mL

Drug Facts

INDICATIONS AND USAGE SECTION:

For Physician Dispensary Only

An effective lightening creme that diminish facial and body discolorations.
DIRECTIONS:
Apply to affected areas in the evening. Apply a sunblock during the day, or as directed by a physician.
Paraben-free
Contains Vitamin C and E

ACTIVE INGREDIENTS:

Hydroquinone 4%

INACTIVE INGREDIENTS:

Water, Glyceryl Monostearate, Polyoxyl 100 Stearate, Butylene Glycol, Stearyl Alcohol, Stearic Acid, Caprylic and Capric Triglyceride, Linoleic Acid, Soy Phospholipids, Dimethicone, C12-15 Alkyl Benzoate, Xanthan Gum, Magnesium Aluminum Silicate, Cetyl Alcohol, Stearyl Alcohol, Glycerin, Licorice, Phenoxyethanol, Ethylhexylglycerin, Hexylene Glycol, Lactic Acid, Disodium EDTA, Dipotassium Glycyrrizinate, Vitamin E, Sodium Metabisulfite, Fragrance-Orange.

WARNING:

For external use only.

Keep out of reach of children

PACKAGE LABEL

DISTRIBUTOR:

Image International

Palm Beach, FL 33411 USA

IMAGE OF PRINCIPAL DISPLAY PANEL: